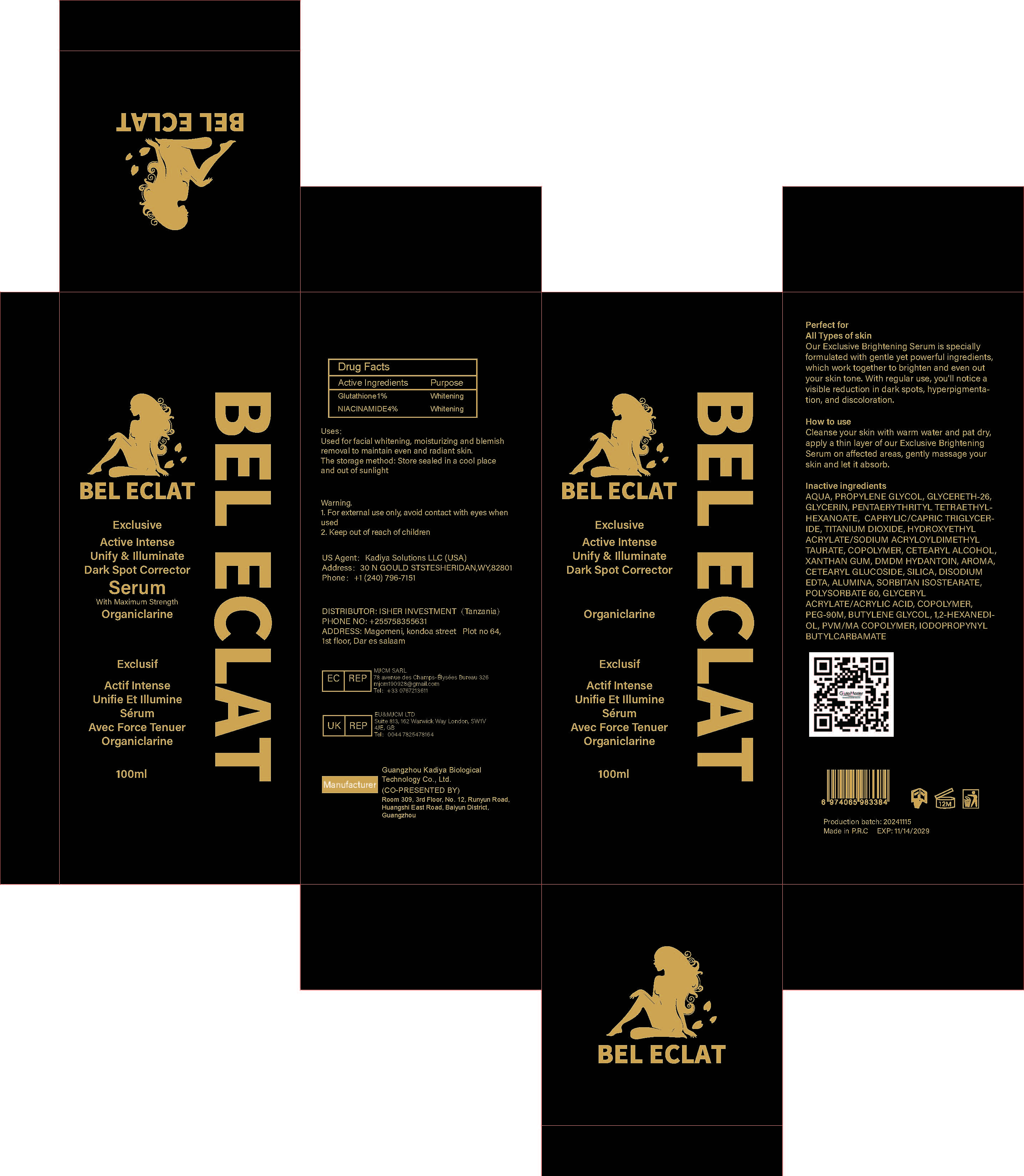 DRUG LABEL: Dark Spot Corrector Serum
NDC: 84423-073 | Form: CREAM, AUGMENTED
Manufacturer: Guangzhou Kadiya Biotechnology Co., Ltd.
Category: otc | Type: HUMAN OTC DRUG LABEL
Date: 20250217

ACTIVE INGREDIENTS: NIACINAMIDE 5 g/100 mL; GLUTATHIONE 1 g/100 mL
INACTIVE INGREDIENTS: GLYCERYL ACRYLATE/ACRYLIC ACID COPOLYMER (300000 CP AT 2%); DMDM HYDANTOIN; EDETATE DISODIUM; 1,2-HEXANEDIOL; AQUA; SILICA; IODOPROPYNYL BUTYLCARBAMATE; PROPYLENE GLYCOL; SORBITAN ISOSTEARATE; METHYL VINYL ETHER AND MALEIC ANHYDRIDE COPOLYMER (1100000 WAMW); POLYSORBATE 60; PEG-90M; BUTYLENE GLYCOL; XANTHAN GUM; CETEARYL GLUCOSIDE; GLYCERETH-26; PENTAERYTHRITYL TETRAETHYLHEXANOATE; TITANIUM DIOXIDE; SALICYLIC ACID; CAPRYLIC/CAPRIC TRIGLYCERIDE; HYDROXYETHYL ACRYLATE/SODIUM ACRYLOYLDIMETHYL TAURATE COPOLYMER (45000 MPA.S AT 1%); GLYCERIN; CETEARYL ALCOHOL; ALUMINA

PURPOSE

Used for facial whitening, moisturizing and blemish removal to maintain even and radiant skin.

INACTIVE INGREDIENT

AQUA，PROPYLENE GLYCOL，GLYCERETH-26，GLYCERIN，PENTAERYTHRITYL TETRAETHYLHEXANOATE， CAPRYLIC/CAPRIC TRIGLYCERIDE，TITANIUM DIOXIDE，HYDROXYETHYL ACRYLATE/SODIUM ACRYLOYLDIMETHYL TAURATE，COPOLYMER，CETEARYL ALCOHOL，XANTHAN GUM，DMDM HYDANTOIN，AROMA，CETEARYL GLUCOSIDE，SILICA，DISODIUM EDTA，ALUMINA，SORBITAN ISOSTEARATE，POLYSORBATE 60，GLYCERYL ACRYLATE/ACRYLIC ACID，COPOLYMER，PEG-90M，BUTYLENE GLYCOL，1,2-HEXANEDIOL，PVM/MA COPOLYMER，IODOPROPYNYL BUTYLCARBAMATE

Warning.
1、For external use only, avoid contact with eyes when used
2、Keep out of reach of children

INACTIVE INGREDIENT

Used for facial whitening, moisturizing and blemish removal to maintain even and radiant skin.

DOSAGE AND ADMINISTRATION

Cleanse your skin with warm water and pat dry apply a thin layer of our Exdlusive Brightening Serum on affected areas, gently massage your skin and let it absorb.

KEEP OUT OF REACH OF CHILDREN SECTION

Active Ingredients
Glutathione1%
NIACINAMIDE4%

INDICATIONS AND USAGE

Cleanse your skin with warm water and pat dry,apply a thin layer of our Exclusive Brightening Serum on affected areas, gently massage your skin and let it absorb.

PACKAGE LABEL

Active Ingredients
Glutathione1%
NIACINAMIDE4%

Uses：
Used for facial whitening, moisturizing and blemish removal to maintain even and radiant skin.
The storage method：
Store sealed in a cool place and out of sunlight

Warning.
1、For external use only, avoid contact with eyes when used
2、Keep out of reach of children

Inactive ingredients：
AQUA，PROPYLENE GLYCOL，GLYCERETH-26，GLYCERIN，PENTAERYTHRITYL TETRAETHYLHEXANOATE， CAPRYLIC/CAPRIC TRIGLYCERIDE，TITANIUM DIOXIDE，HYDROXYETHYL ACRYLATE/SODIUM ACRYLOYLDIMETHYL TAURATE，COPOLYMER，CETEARYL ALCOHOL，XANTHAN GUM，DMDM HYDANTOIN，AROMA，CETEARYL GLUCOSIDE，SILICA，DISODIUM EDTA，ALUMINA，SORBITAN ISOSTEARATE，POLYSORBATE 60，GLYCERYL ACRYLATE/ACRYLIC ACID，COPOLYMER，PEG-90M，BUTYLENE GLYCOL，1,2-HEXANEDIOL，PVM/MA COPOLYMER，IODOPROPYNYL BUTYLCARBAMATE